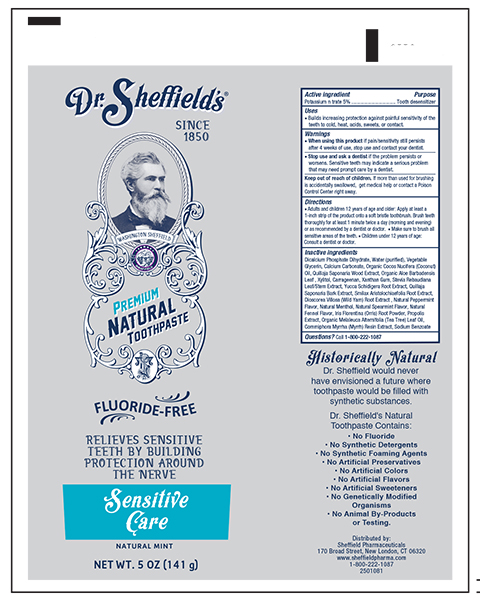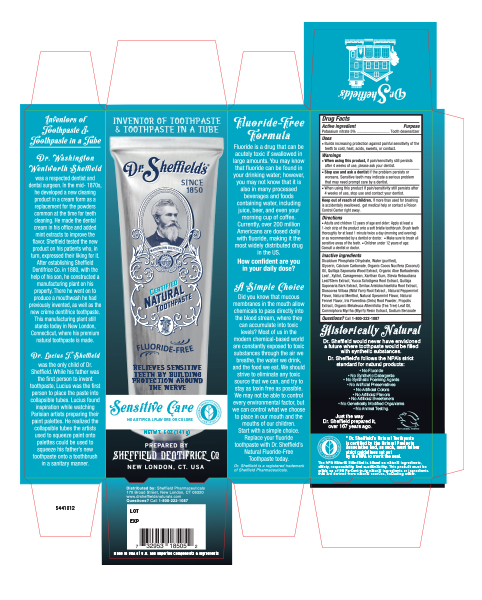 DRUG LABEL: Dr. Sheffield Sensitive Care
NDC: 11527-420 | Form: PASTE, DENTIFRICE
Manufacturer: Sheffield Pharmaceuticals LLC
Category: otc | Type: HUMAN OTC DRUG LABEL
Date: 20231130

ACTIVE INGREDIENTS: POTASSIUM NITRATE 50 mg/1 g
INACTIVE INGREDIENTS: CALCIUM PHOSPHATE, DIBASIC, DIHYDRATE; WATER; GLYCERIN; CALCIUM CARBONATE; COCONUT OIL; QUILLAJA SAPONARIA WOOD; ALOE VERA LEAF; XYLITOL; CARRAGEENAN; XANTHAN GUM; STEVIA REBAUDIUNA LEAF; YUCCA SCHIDIGERA ROOT; SMILAX ARISTOLOCHIIFOLIA ROOT; DIOSCOREA VILLOSA ROOT; IRIS GERMANICA VAR. FLORENTINA ROOT; PROPOLIS WAX; MELALEUCA ALTERNIFOLIA LEAF; COMMIPHORA MYRRHA TOP

Dr. Sheffield Sensitive Care

Active Ingredient

Potassium Nitrate 5%

Purpose

Tooth desensitizer

Uses

Builds increasing protection against painful sensitivity of the teeth to cold, heat, acids, sweets or contact.

Warnings

When using this product, if pain/sensivity still persists after 4 weeks of use, please ask your dentist.

Stop Use and ask a Dentist, if the problem persists or worsens, Sensitive teeth may indicate a serious problem that may neeed prompt care of a dentist.

When using this product, if pain/sensivity still persists after 4 weeks of use, stop use and contact your dentist.

KEEP OUT OF REACH OF CHILDREN

Keep out of the reach of Children, If more than used for brushing is accidently swallowed, get medical help or contact a Poison Control Center right away.

Directions

Adults and children 12 years of age and older: Apply at least a 1 inch strip of the product onto a soft bristle toothbrush. Brush teeth thoroughly for at least 1 minute twice a day (morning and evening) or as recommended by a dentist or doctor.
Make sure to brush all sensitive areas of the teeth.
Children under 12 years of age: consult a dentist or doctor.

Inactive ingredients

Dicalcium Phosphate Dihydrate, Water (purified), Glycerin, Calcium Carbonate, Organic Cocos Nucifera (Coconut) oil, Quillaja Saponaria Wood Extract, Organic Aloe Barbadensis Leaf, Xylitol, Carrageenan, Xanthum Gum, Stevia Rebaudiana Leaf/Stem Extract, Yucca Schidigera Root extract, Quillaja Saponaria Bark Extract, Smilax Aristolochiaefolia Root extract, Dioscorea Villosa (Wild Yam) Root extract, Natural Peppermint flavor, Natural Menthol, Natural Spearmint Flavor, Natural Fennel Flavor, Iris Florentina (Orris) Root Powder, Propolis Extract, Organic Melaleuca Alternifolia(teatree) oil, Commiphora Myrrha (Myrrha) ResinExtract, Sodium Benzoate

Principal Primary Panel Tube 5.0 oz

Dr. Sheffield Certifed Natural Toothpaste

Sensitive Care Natural Mint

NET WT. 5 OZ (141g)

Principal Primary Panel Carton 5.0 oz

Dr. Sheffield Certifed Natural Tooth Paste

Sensitive Care Natural Mint Flavor

NET WT. 5 oz (141g)